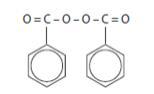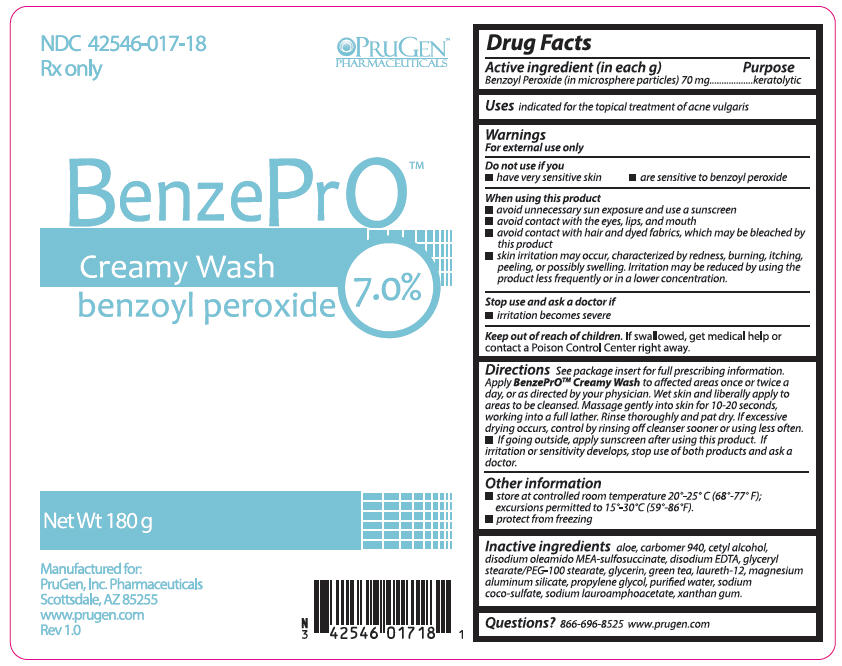 DRUG LABEL: BenzePrO Creamy Wash
NDC: 42546-017 | Form: SOAP
Manufacturer: PruGen, Inc.
Category: prescription | Type: HUMAN PRESCRIPTION DRUG LABEL
Date: 20180705

ACTIVE INGREDIENTS: BENZOYL PEROXIDE 7 g/100 g
INACTIVE INGREDIENTS: ALOE; CARBOMER HOMOPOLYMER TYPE C (ALLYL PENTAERYTHRITOL CROSSLINKED); CETYL ALCOHOL; DISODIUM OLEAMIDO MONOETHANOLAMINE SULFOSUCCINATE; EDETATE DISODIUM; GLYCERIN; GREEN TEA LEAF; LAURETH-12; MAGNESIUM ALUMINUM SILICATE; PROPYLENE GLYCOL; WATER; SODIUM COCO-SULFATE; SODIUM LAUROAMPHOACETATE; XANTHAN GUM

BenzePrO Creamy Wash

BenzePro™ Creamy Wash benzoyl peroxide 7.0%
PruGen, Inc. Pharmaceuticals

DESCRIPTION:

BenzePrOTM Creamy Wash is intended for topical administration and contains Benzoyl Peroxide for use in the treatment of acne vulgaris. Benzoyl Peroxide is an oxidizing agent that possesses antibacterial properties and is classified as a keratolytic. Benzoyl Peroxide (C14H10O4) is represented by the following chemical structure:

Each gram of BenzePrOTM Creamy Wash contains 70 mg of Benzoyl Peroxide as microsphere particles (via Curoxyl® 42) in an emulsion based formulation consisting of: aloe, carbomer 940, cetyl alcohol, disodium oleamido MEA-sulfosuccinate, disodium EDTA, glyceryl stearate/PEG-100 stearate, glycerin, green tea, laureth-12, magnesium aluminum silicate, propylene glycol, purified water, sodium coco-sulfate, sodium lauroamphoacetate, xanthan gum.

CLINICAL PHARMACOLOGY:

The mechanism of action of Benzoyl Peroxide is not totally understood but its antibacterial activity against Propionibacterium acnes is thought to be a major mode of action. In addition, patients treated with Benzoyl Peroxide show a reduction in lipids and free fatty acids, and mild desquamation (drying and peeling activity) with simultaneous reduction in comedones and acne lesions. Little is known about the percutaneous penetration, metabolism, and excretion of Benzoyl Peroxide, although it has been shown that Benzoyl Peroxide absorbed by the skin is metabolized to benzoic acid and then excreted as benzoate in the urine. There is no evidence of systemic toxicity caused by Benzoyl Peroxide in humans.

INDICATIONS AND USAGE:

BenzePrOTM Creamy Wash is indicated for the topical treatment of acne vulgaris.

CONTRAINDICATIONS:

BenzePrOTM Creamy Wash is contraindicated in persons with a known hypersensitivity to any of its ingredients.

WARNINGS:

Do not use if you:

- have very sensitive skin
- are sensitive to benzoyl peroxide

When using this product:

- avoid unnecessary sun exposure and use a sunscreen
- avoid contact with the eyes, lips, and mouth
- avoid contact with hair and dyed fabrics, which may be bleached by this product
- skin irritation may occur, characterized by redness, burning, itching, peeling, or possibly swelling. Irritation may be reduced by using the product less frequently or in a lower concentration.

Stop use and ask a doctor if:

- irritation becomes severe

PRECAUTIONS:

For external use only. If severe irritation develops, discontinue use and institute appropriate therapy. After reaction clears, treatment may often be resumed with less frequent application. These preparations should not be used in or near the eyes or on mucous membranes.

INFORMATION FOR PATIENTS:

General: If accidental contact occurs with eyes, mouth, or mucous membranes, rinse with water.

Carcinogensesis, Mutagenesis, Impairment of Fertility:

Data from several studies employing a strain of mice that is highly susceptible to developing cancer suggest that Benzoyl Peroxide acts as a tumor promoter. The clinical significance of these findings to humans is unknown. Benzoyl Peroxide has not been found to be mutagenic (Ames Test) and there are no published data indicating it impairs fertility.

Pregnancy:

Teratogenic Effects: Pregnancy Category C: Animal reproduction studies have not been conducted with Benzoyl Peroxide. It is not known whether Benzoyl Peroxide can cause fetal harm when administered to a pregnant woman or can affect reproduction capacity. Benzoyl Peroxide should be used by a pregnant woman only if clearly needed. There are no available data on the effect of Benzoyl Peroxide on the later growth, development and functional maturation of the unborn child.

Nursing Mothers:

It is not known whether this drug is excreted in human milk. Because many drugs are excreted in human milk, caution should be exercised when Benzoyl Peroxide is administered to a nursing woman.

Pediatric Use:

Safety and effectiveness in children have not been established.

ADVERSE REACTIONS:

Allergic contact dermatitis and dryness have been reported with topical Benzoyl Peroxide therapy.

OVERDOSAGE:

If excessive scaling, erythema or edema occurs, the use of this preparation should be discontinued. To hasten resolution of the adverse effects, cool compresses may be used. After symptoms and signs subside, a reduced dosage schedule may be cautiously tried if the reaction is judged to be due to excessive use and not allergenicity.

DOSAGE AND ADMINISTRATION:

BenzePrOTM Creamy Wash: Apply to affected areas once or twice a day, or as directed by your physician. Wet skin and liberally apply to areas to be cleansed. Massage gently into skin for 10-20 seconds, working into a full lather. Rinse thoroughly and pat dry. If excessive drying occurs, control by rinsing off cleanser sooner or using less often.

- If going outside, apply sunscreen after using this product. If irritation or sensitivity develops, stop use of both products and ask a doctor.

HOW SUPPLIED:

BenzePrO™ Creamy Wash is supplied in a 180 g bottle (NDC 42546-017-18).

Store at controlled room temperature 20°-25° C (68°-77° F); excursions permitted to 15°-30°C (59°-86°F).

Protect from freezing.

KEEP THIS AND ALL MEDICATIONS OUT OF THE REACH OF CHILDREN.

Manufactured for:
PruGen, Inc. Pharmaceuticals
18899 North Thompson Peak Parkway
Scottsdale, AZ 85255

PRINCIPAL DISPLAY PANEL - 180 g Tube Label

NDC 42546-017-18
Rx only

PRUGEN™
PHARMACEUTICALS

BenzePrO™

Creamy Wash

benzoyl peroxide
7.0%

Net Wt 180 g

Manufactured for:
PruGen, Inc. Pharmaceuticals
Scottsdale, AZ 85255
www.prugen.com
Rev 1.1